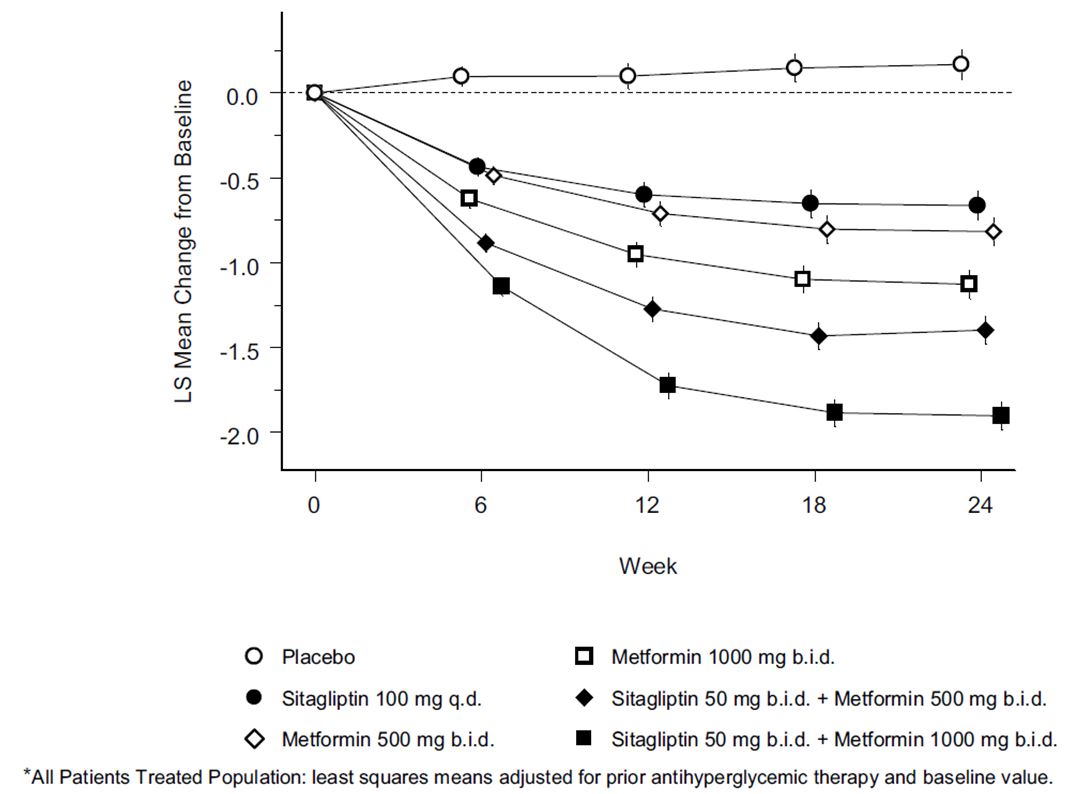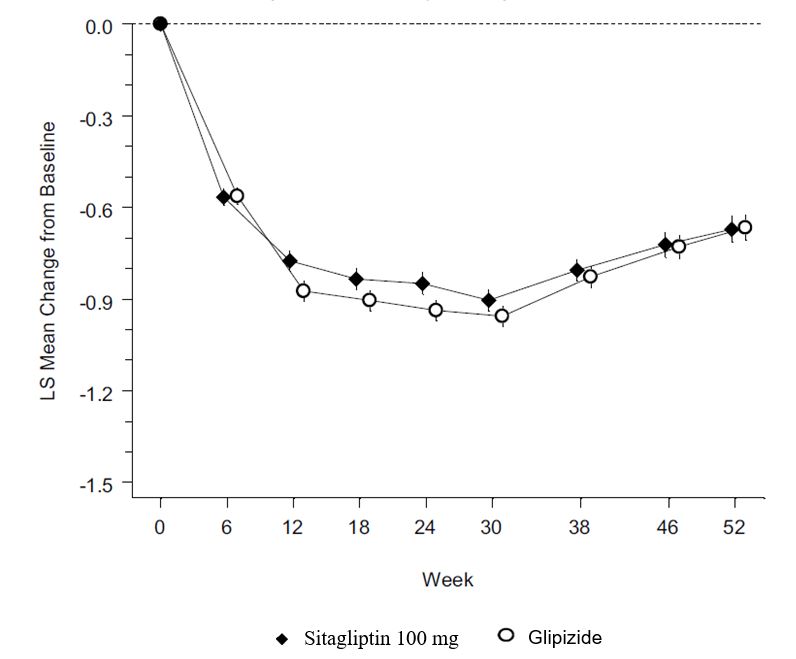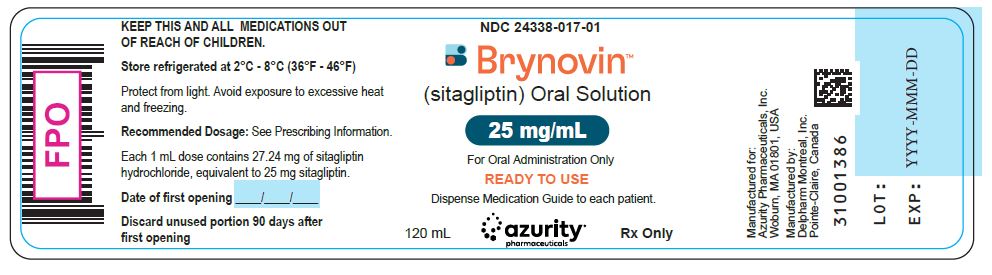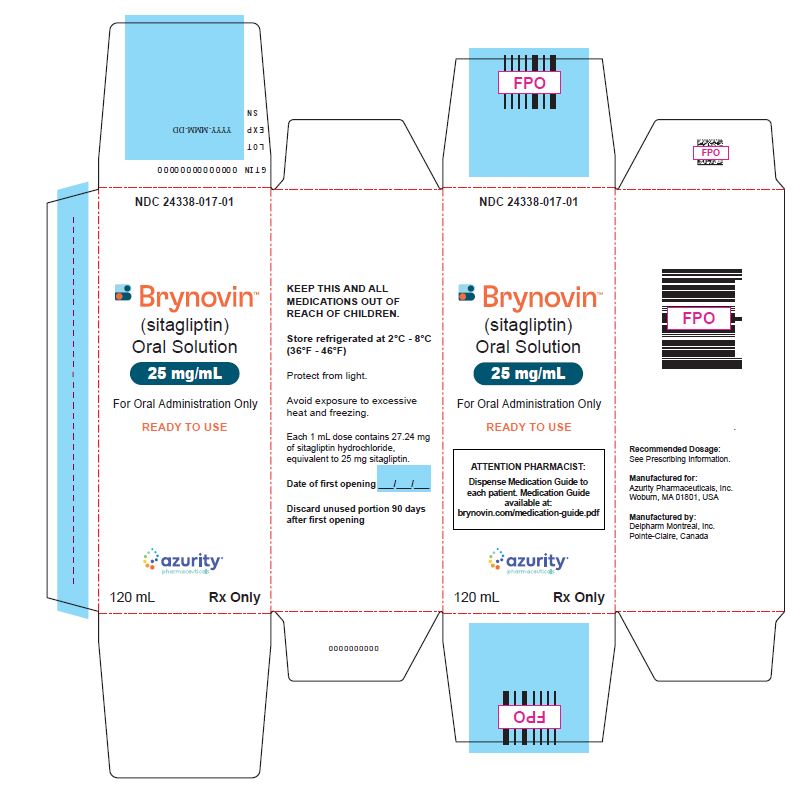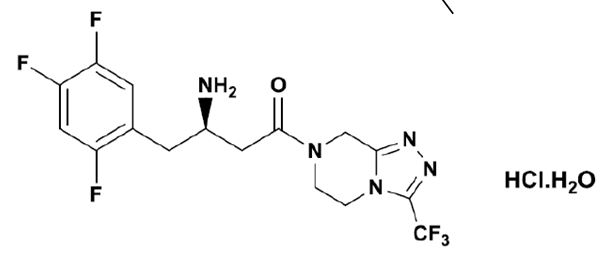 DRUG LABEL: BRYNOVIN
NDC: 24338-017 | Form: SOLUTION
Manufacturer: Azurity Pharmaceuticals, Inc.
Category: prescription | Type: Human Prescription Drug Label
Date: 20250102

ACTIVE INGREDIENTS: SITAGLIPTIN 25 mg/1 mL
INACTIVE INGREDIENTS: BUTYLATED HYDROXYANISOLE; EDETATE DISODIUM; SODIUM CITRATE; METHYLPARABEN SODIUM; ANHYDROUS CITRIC ACID; POLYSORBATE 80; HYDROXYETHYL CELLULOSE, UNSPECIFIED; WATER

HIGHLIGHTS OF PRESCRIBING INFORMATION

These highlights do not include all the information needed to use BRYNOVINTM safely and effectively. See full prescribing information for BRYNOVINTM.
BRYNOVINTM (sitagliptin) oral solution
Initial U.S. Approval: 2006

1 INDICATIONS & USAGE

BRYNOVIN is a dipeptidyl peptidase-4 (DPP-4) inhibitor indicated as an adjunct to diet and exercise to improve glycemic control in adults with type 2 diabetes mellitus. (1)
Limitations of Use:
• BRYNOVIN is not recommended in patients with type 1 diabetes. (1)
• BRYNOVIN has not been studied in patients with a history of pancreatitis. (1)

2 DOSAGE & ADMINISTRATION

The recommended dose of BRYNOVIN is 100 mg orally once daily (4 mL). BRYNOVIN can be taken with or without food. (2.1)
Dosage adjustment is recommended for patients with eGFR less than 45 mL/min/1.73 m^2. (2.2)

Dosage Adjustment in Patients with Renal Impairment (2.2)
eGFR greater than or equal to 30 mL/min/1.73 m^2 to less than 45 mL/min/1.73 m^2 | eGFR less than 30 mL/min/1.73 m^2 (including patients with end stage renal disease [ESRD] on dialysis)
50 mg once daily (2 mL) | 25 mg once daily (1 mL)

3 DOSAGE FORMS & STRENGTHS

Oral solution: 25 mg per mL (3)

4 CONTRAINDICATIONS

History of a serious hypersensitivity reaction to sitagliptin or any of the excipients in BRYNOVIN, such as anaphylaxis or angioedema. (4)

5 WARNINGS AND PRECAUTIONS

• Pancreatitis: There have been postmarketing reports of acute pancreatitis, including fatal and non-fatal hemorrhagic or necrotizing pancreatitis. If pancreatitis is suspected, promptly discontinue BRYNOVIN. (5.1)
• Heart failure: Heart failure has been observed with two other members of the DPP-4 inhibitor class. Consider risks and benefits of BRYNOVIN in patients who have known risk factors for heart failure. Monitor patients for signs and symptoms. (5.2)
• Acute Renal Failure: Has been reported postmarketing, sometimes requiring dialysis. Assessment of renal function is recommended prior to initiating BRYNOVIN and periodically thereafter. (5.3)
• Hypoglycemia with Concomitant Use with Insulin or Insulin Secretagogues: Increased risk of hypoglycemia when used in combination with insulin or an insulin secretagogue. Lower dose of insulin or insulin secretagogue may be required. (5.4)
• Hypersensitivity Reactions: There have been postmarketing reports of serious allergic and hypersensitivity reactions in patients treated with sitagliptin such as anaphylaxis, angioedema, and exfoliative skin conditions including Stevens-Johnson syndrome. Promptly stop BRYNOVIN, assess for other potential causes, institute appropriate monitoring and treatment. (5.5)
• Severe and Disabling Arthralgia: Has been reported in patients taking DPP-4 inhibitors. Consider as a possible cause for severe joint pain and discontinue drug if appropriate. (5.6)
• Bullous Pemphigoid: There have been postmarketing reports requiring hospitalization in patients taking DPP-4 inhibitors. Tell patients to report development of blisters or erosions. If bullous pemphigoid is suspected, discontinue BRYNOVIN. (5.7)

6 ADVERSE REACTIONS

Most common adverse reactions (incidence ≥5%) are: upper respiratory tract infection, nasopharyngitis and headache. In the add-on to sulfonylurea and add-on to insulin trials, hypoglycemia was also more commonly reported in patients treated with sitagliptin compared to placebo. (6.1)
To report SUSPECTED ADVERSE REACTIONS, contact Azurity Pharmaceuticals, Inc., at 1-800-461-7449 or FDA at 1-800-FDA-1088 or www.fda.gov/medwatch.

FULL PRESCRIBING INFORMATION

1 INDICATIONS & USAGE

BRYNOVIN is indicated as an adjunct to diet and exercise to improve glycemic control in adults with type 2 diabetes mellitus.

Limitations of Use

BRYNOVIN is not recommended in patients with type 1 diabetes.
BRYNOVIN has not been studied in patients with a history of pancreatitis. It is unknown whether patients with a history of pancreatitis are at increased risk for the development of pancreatitis while using BRYNOVIN. [see Warnings and Precautions (5.1)].

2 DOSAGE & ADMINISTRATION

2.1 Recommended Dosage and Administration

Measure the BRYNOVIN dose using a calibrated oral syringe or oral dosing cup scored using metric units of measurements (i.e., mL).
The recommended dosage of BRYNOVIN is 100 mg (4 mL) taken orally once daily. BRYNOVIN can be taken with or without food [see Clinical Pharmacology (12.3)].

2.2 Recommendations for Use in Renal Impairment

Assess renal function prior to initiation of BRYNOVIN and periodically thereafter [see Use in Specific Populations (8.6)].
For patients with an estimated glomerular filtration rate (eGFR) greater than or equal to 45 mL/min/1.73 m^2 to less than 90 mL/min/1.73 m^2, no dosage adjustment for BRYNOVIN is required.
For patients with moderate renal impairment (eGFR greater than or equal to 30 mL/min/1.73 m^2 to less than 45 mL/min/1.73 m^2), the dosage of BRYNOVIN is 50 mg (2 mL) once daily.
For patients with severe renal impairment (eGFR less than 30 mL/min/1.73 m^2) or with end-stage renal disease (ESRD) requiring hemodialysis or peritoneal dialysis, the dosage of BRYNOVIN is 25 mg (1 mL) once daily. BRYNOVIN may be administered without regard to the timing of dialysis.

3 DOSAGE FORMS & STRENGTHS

BRYNOVIN oral solution 25 mg/mL is supplied as a clear, colorless to nearly colorless aqueous solution in an amber glass bottle.

4 CONTRAINDICATIONS

BRYNOVIN is contraindicated in patients with a history of a serious hypersensitivity reaction to sitagliptin or any of the excipients in BRYNOVIN. Serious hypersensitivity reactions, including anaphylaxis and angioedema have been reported [see Warnings and Precautions (5.5) and Adverse Reactions (6.2)].

5 WARNINGS AND PRECAUTIONS

5.1 Pancreatitis

There have been postmarketing reports of acute pancreatitis, including fatal and non-fatal hemorrhagic or necrotizing pancreatitis, in patients taking sitagliptin. After initiation of BRYNOVIN, patients should be observed carefully for signs and symptoms of pancreatitis. If pancreatitis is suspected, BRYNOVIN should promptly be discontinued and appropriate management should be initiated. It is unknown whether patients with a history of pancreatitis are at increased risk for the development of pancreatitis while using BRYNOVIN.

5.2 Heart Failure

An association between dipeptidyl peptidase-4 (DPP-4) inhibitor treatment and heart failure has been observed in cardiovascular outcomes trials for two other members of the DPP-4 inhibitor class. These trials evaluated patients with type 2 diabetes mellitus and atherosclerotic cardiovascular disease.
Consider the risks and benefits of BRYNOVIN prior to initiating treatment in patients at risk for heart failure, such as those with a prior history of heart failure and a history of renal impairment, and observe these patients for signs and symptoms of heart failure during therapy. Advise patients of the characteristic symptoms of heart failure and to immediately report such symptoms. If heart failure develops, evaluate and manage according to current standards of care and consider discontinuation of BRYNOVIN.

5.3 Acute Renal Failure

There have been postmarketing reports of worsening renal function, including acute renal failure, sometimes requiring dialysis with sitagliptin. A subset of these reports involved patients with renal impairment, some of whom were prescribed inappropriate dosages of sitagliptin. A return to baseline levels of renal impairment has been observed with supportive treatment and discontinuation of potentially causative agents. Consideration can be given to cautiously reinitiating BRYNOVIN if another etiology is deemed likely to have precipitated the acute worsening of renal function.
Assessment of renal function is recommended prior to initiating BRYNOVIN and periodically thereafter. A dosage adjustment is recommended in patients with moderate or severe renal impairment and in patients with ESRD requiring hemodialysis or peritoneal dialysis. [see Dosage and Administration (2.2) and Use in Specific Populations (8.6)].

5.4 Hypoglycemia with Concomitant Use with Insulin or Insulin Secretagogues

When BRYNOVIN was used in combination with insulin or insulin secretagogues (e.g., sulfonylurea), medications known to cause hypoglycemia, the incidence of hypoglycemia was increased over that of placebo [see Adverse Reactions (6.1)]. Therefore, a lower dosage of insulin or sulfonylurea may be required to reduce the risk of hypoglycemia when used in combination with BRYNOVIN. [see Drug Interactions (7.1)]. Inform patients using these concomitant medications of the risk of hypoglycemia and educate them on the signs and symptoms of hypoglycemia.

5.5 Hypersensitivity Reactions

There have been postmarketing reports of serious hypersensitivity reactions in patients treated with sitagliptin. These reactions include anaphylaxis, angioedema, and exfoliative skin conditions including Stevens-Johnson syndrome. Onset of these reactions occurred within the first 3 months after initiation of treatment with sitagliptin, with some reports occurring after the first dose. If a hypersensitivity reaction is suspected, discontinue BRYNOVIN, assess for other potential causes for the event, and institute alternative treatment for diabetes. [see Adverse Reactions (6.2)].
Angioedema has also been reported with other DPP-4 inhibitors. Use caution in a patient with a history of angioedema with another DPP-4 inhibitor because it is unknown whether such patients will be predisposed to angioedema with BRYNOVIN.

5.6 Severe and Disabling Arthralgia

There have been postmarketing reports of severe and disabling arthralgia in patients taking DPP-4 inhibitors. The time to onset of symptoms following initiation of drug therapy varied from one day to years. Patients experienced relief of symptoms upon discontinuation of the medication. A subset of patients experienced a recurrence of symptoms when restarting the same drug or a different DPP-4 inhibitor. Consider DPP-4 inhibitors as a possible cause for severe joint pain and discontinue the drug if appropriate.

5.7 Bullous Pemphigoid

Postmarketing cases of bullous pemphigoid requiring hospitalization have been reported with DPP- 4 inhibitor use. In reported cases, patients typically recovered with topical or systemic immunosuppressive treatment and discontinuation of the DPP-4 inhibitor. Tell patients to report development of blisters or erosions while receiving BRYNOVIN. If bullous pemphigoid is suspected, BRYNOVIN should be discontinued and referral to a dermatologist should be considered for diagnosis and appropriate treatment.

6 ADVERSE REACTIONS

The following adverse reactions are also discussed elsewhere in the labeling:
• Pancreatitis [see Warnings and Precautions (5.1)]
• Heart Failure [see Warnings and Precautions (5.2)]
• Acute Renal Failure [see Warnings and Precautions (5.3)]
• Hypoglycemia with Concomitant Use with Insulin or Insulin Secretagogues [see Warnings and Precautions (5.4)]
• Hypersensitivity Reactions [see Warnings and Precautions (5.5)]
• Severe and Disabling Arthralgia [see Warnings and Precautions (5.6)]
• Bullous Pemphigoid [see Warnings and Precautions (5.7)]

6.1 Clinical Trials Experience

Because clinical trials are conducted under widely varying conditions, adverse reaction rates observed in the clinical trials of a drug cannot be directly compared to rates in the clinical trials of another drug and may not reflect the rates observed in practice.
The safety of BRYNOVIN has been established for glycemic control in patients with type 2 diabetes mellitus based in adequate and well-controlled trials of sitagliptin tablets, referenced below as “sitagliptin” [see Clinical Studies (14)].
Common Adverse Reactions
In controlled clinical trials as both monotherapy and combination therapy with metformin, pioglitazone, or rosiglitazone and metformin, the overall incidence of adverse reactions, hypoglycemia, and discontinuation of therapy due to clinical adverse reactions with sitagliptin were similar to placebo. In combination with glimepiride, with or without metformin, the overall incidence of clinical adverse reactions with sitagliptin was higher than with placebo, in part related to a higher incidence of hypoglycemia (see Table 3); the incidence of discontinuation due to clinical adverse reactions was similar to placebo.
Two placebo-controlled monotherapy trials, one of 18- and one of 24-week duration, included patients treated with sitagliptin 100 mg daily, sitagliptin 200 mg daily, and placebo. Five placebo-controlled add-on combination therapy trials were also conducted: one with metformin; one with pioglitazone; one with metformin and rosiglitazone; one with glimepiride (with or without metformin); and one with insulin (with or without metformin). In these trials, patients with inadequate glycemic control on a stable dosage of the background therapy were randomized to add-on therapy with sitagliptin 100 mg daily or placebo. The adverse reactions, excluding hypoglycemia, in ≥5% of patients treated with sitagliptin 100 mg daily and more commonly than in patients treated with placebo, are shown in Table 1 for the clinical trials of at least 18 weeks duration. Incidences of hypoglycemia are shown in Table 3.
Table 1:Placebo-Controlled Clinical Trials of Sitagliptin Monotherapy or Add-on Combination Therapy with Pioglitazone, Metformin + Rosiglitazone, or Glimepiride +/- Metformin: Adverse Reactions (Excluding Hypoglycemia) Reported in ≥5% of Patients and More Commonly than in Patients Given Placebo*

 | Number of Patients (%)
Monotherapy (18 or 24 weeks) | Sitagliptin 100 mg | Placebo
 | N = 443 | N = 363
Nasopharyngitis | 23 (5.2) | 12 (3.3)
Combination with Pioglitazone (24 weeks) | Sitagliptin 100 mg + Pioglitazone | Placebo + Pioglitazone
 | N = 175 | N = 178
Upper Respiratory Tract Infection | 11 (6.3) | 6 (3.4)
Headache | 9 (5.1) | 7 (3.9)
Combination with Metformin + Rosiglitazone (18 weeks) | Sitagliptin 100 mg + Metformin + Rosiglitazone | Placebo + Metformin + Rosiglitazone
 | N = 181 | N = 97
Upper Respiratory Tract Infection | 10 (5.5) | 5 (5.2)
Nasopharyngitis | 11 (6.1) | 4 (4.1)
Combination with Glimepiride (+/- Metformin) (24 weeks) | Sitagliptin 100 mg + Glimepiride (+/- Metformin) | Placebo + Glimepiride (+/- Metformin)
 | N = 222 | N = 219
Nasopharyngitis | 14 (6.3) | 10 (4.6)
Headache | 13 (5.9) | 5 (2.3)

* Intent-to-treat population
In the 24-week trial of patients receiving sitagliptin as add-on combination therapy with metformin, there were no adverse reactions reported in patients and more commonly than in patients given placebo.
In the 24-week trial of patients receiving sitagliptin as add-on therapy to insulin (with or without metformin), there were no adverse reactions reported in patients and more commonly than in patients given placebo, except for hypoglycemia (see Table 3).
In the trial of sitagliptin as add-on combination therapy with metformin and rosiglitazone (Table 1), through Week 54 the adverse reactions in patients treated with sitagliptin and more commonly than in patients treated with placebo were: upper respiratory tract infection (sitagliptin, 15.5%; placebo, 6.2%), nasopharyngitis (11%, 9.3%), peripheral edema (8.3%, 5.2%), and headache (5.5%, 4.1%).
In an additional, 24-week, placebo-controlled factorial trial of initial therapy with sitagliptin in combination with metformin, the adverse reactions reported in ≥5% of patients are shown in Table 2.
Table 2:Initial Therapy with Combination of Sitagliptin and Metformin: Adverse Reactions Reported in ≥5% of Patients Receiving Combination Therapy (and Greater than in Patients Receiving Metformin alone, Sitagliptin alone, and Placebo)*

 | Number of Patients (%)
 | Placebo | Sitagliptin 100 mg QD | Metformin HCl 500 or 1,000 mg bid† | Sitagliptin 50 mg bid + Metformin HCl 500 or 1,000 mg bid†
 | N = 176 | N = 179 | N = 364† | N = 372†
Upper Respiratory Infection | 9 (5.1) | 8 (4.5) | 19 (5.2) | 23 (6.2)
Headache | 5 (2.8) | 2 (1.1) | 14 (3.8) | 22 (5.9)

* Intent-to-treat population.
† Data pooled for the patients given the lower and higher dosages of metformin.

In a 24-week trial of initial therapy with sitagliptin in combination with pioglitazone, there were no adverse reactions reported in ≥5% of patients and more commonly than in patients given pioglitazone alone.
Other Adverse Reactions
Hypoglycemia
In the above trials (N=9), adverse reactions of hypoglycemia were based on all reports of symptomatic hypoglycemia. A concurrent blood glucose measurement was not required although most (74%) reports of hypoglycemia were accompanied by a blood glucose measurement ≤70 mg/dL. When sitagliptin was coadministered with a sulfonylurea or with insulin, the percentage of patients with at least one adverse reaction of hypoglycemia was higher than in the corresponding placebo group (Table 3).
Table 3:Incidence and Rate of Hypoglycemia* in Placebo-Controlled Clinical Trials when Sitagliptin was used as Add-On Therapy to Glimepiride (with or without Metformin) or Insulin (with or without Metformin)

Add-On to Glimepiride (+/- Metformin) (24 weeks) | Sitagliptin 100 mg + Glimepiride (+/- Metformin) | Placebo + Glimepiride (+/- Metformin)
 | N = 222 | N = 219
Overall (%) | 27 (12.2) | 4 (1.8)
Rate (episodes/patient-year)† | 0.59 | 0.24
Severe (%)‡ | 0 (0) | 0 (0)
Add-On to Insulin (+/- Metformin) (24 weeks) | Sitagliptin 100 mg + Insulin (+/- Metformin) | Placebo + Insulin (+/- Metformin)
 | N = 322 | N = 319
Overall (%) | 50 (15.5) | 25 (7.8)
Rate (episodes/patient-year)† | 1.06 | 0.51
Severe (%)‡ | 2 (0.6) | 1 (0.3)

* Adverse reactions of hypoglycemia were based on all reports of symptomatic hypoglycemia; a concurrent glucose measurement was not required; intent-to-treat population.
† Based on total number of events (i.e., a single patient may have had multiple events).
‡ Severe events of hypoglycemia were defined as those events requiring medical assistance or exhibiting depressed level/loss of consciousness or seizure.

In a pooled analysis of the two monotherapy trials, the add-on to metformin trial, and the add-on to pioglitazone trial, the overall incidence of adverse reactions of hypoglycemia was 1.2% in patients treated with sitagliptin 100 mg and 0.9% in patients treated with placebo.
In the trial of sitagliptin as add-on combination therapy with metformin and rosiglitazone, the overall incidence of hypoglycemia was 2.2% in patients given add-on sitagliptin and 0% in patients given add-on placebo through Week 18. Through Week 54, the overall incidence of hypoglycemia was 3.9% in patients given add-on sitagliptin and 1% in patients given add-on placebo.
In the 24-week, placebo-controlled factorial trial of initial therapy with sitagliptin in combination with metformin, the incidence of hypoglycemia was 0.6% in patients given placebo, 0.6% in patients given sitagliptin alone, 0.8% in patients given metformin alone, and 1.6% in patients given sitagliptin in combination with metformin.
In the trial of sitagliptin as initial therapy with pioglitazone, one patient taking sitagliptin experienced a severe episode of hypoglycemia. There were no severe hypoglycemia episodes reported in other trials except in the trial involving coadministration with insulin.
In an additional, 30-week placebo-controlled, trial of patients with type 2 diabetes mellitus inadequately controlled with metformin comparing the maintenance of sitagliptin 100 mg versus withdrawal of sitagliptin when initiating basal insulin therapy, the event rate and incidence of documented symptomatic hypoglycemia (blood glucose measurement ≤70 mg/dL) did not differ between the sitagliptin and placebo groups.

Gastrointestinal Adverse Reactions
In a pooled analysis of the two monotherapy trials, the add-on to metformin trial, and the add-on to pioglitazone trial, the incidence of selected gastrointestinal adverse reactions in patients treated with sitagliptin was as follows: abdominal pain (sitagliptin 100 mg, 2.3%; placebo, 2.1%), nausea (1.4%, 0.6%), and diarrhea (3%, 2.3%).
Pancreatitis
In a pooled analysis of 19 double-blind clinical trials that included data from 10,246 patients randomized to receive sitagliptin 100 mg/day (N=5,429) or corresponding (active or placebo) control (N=4,817), the incidence of acute pancreatitis was 0.1 per 100 patient-years in each group (4 patients with an event in 4,708 patient-years for sitagliptin and 4 patients with an event in 3,942 patient-years for control).
Vital Sign and Electrocardiogram (ECG) Changes
No clinically meaningful changes in vital signs or in ECG (including in QTc interval) were observed in patients treated with sitagliptin.
Laboratory Tests
Across clinical trials, the incidence of laboratory adverse reactions was similar in patients treated with sitagliptin 100 mg compared to patients treated with placebo. A small increase in white blood cell count (WBC) was observed due to an increase in neutrophils. This increase in WBC (of approximately 200 cells/microL vs placebo, in four pooled placebo-controlled clinical trials, with a mean baseline WBC count of approximately 6,600 cells/microL) is not considered to be clinically relevant. In a 12-week trial of 91 patients with chronic renal insufficiency, 37 patients with moderate renal insufficiency were randomized to sitagliptin 50 mg daily, while 14 patients with the same magnitude of renal impairment were randomized to placebo. Mean (SE) increases in serum creatinine were observed in patients treated with sitagliptin (0.12 mg/dL [0.04]) and in patients treated with placebo (0.07 mg/dL [0.07]). The clinical significance of this added increase in serum creatinine relative to placebo is not known.

6.2 Postmarketing Experience

The following adverse reactions have been identified during post-approval use of sitagliptin as monotherapy and/or in combination with other antihyperglycemic agents. Because these reactions are reported voluntarily from a population of uncertain size, it is generally not possible to reliably estimate their frequency or establish a causal relationship to drug exposure.
Hypersensitivity Reactions: anaphylaxis, angioedema, rash, urticaria, cutaneous vasculitis, bullous pemphigoid, and exfoliative skin conditions including Stevens-Johnson syndrome
Hepatobiliary disorders: hepatic enzyme elevations
Gastrointestinal disorders: acute pancreatitis, including fatal and non-fatal hemorrhagic and necrotizing pancreatitis, constipation; vomiting, mouth ulceration, and stomatitis
Renal and urinary disorders: worsening renal function, including acute renal failure (sometimes requiring dialysis), and tubulointerstitial nephritis
Musculoskeletal and connective tissue disorders: severe and disabling arthralgia; myalgia; pain in extremity; back pain; pruritus; rhabdomyolysis
Nervous system disorders: headache

7 DRUG INTERACTIONS

7.1 Concomitant Use with Insulin or Insulin Secretagogues

BRYNOVIN lowers blood glucose in patients with type 2 diabetes mellitus. Coadministration of BRYNOVIN with insulin or an insulin secretagogue (e.g., sulfonylurea) or insulin may require lower dosages of the insulin secretagogue or insulin to reduce the risk of hypoglycemia. [See Warnings and Precautions (5.4)].

8 USE IN SPECIFIC POPULATIONS

8.1 Pregnancy

Risk Summary
The limited available data with sitagliptin in pregnant women are not sufficient to inform a drug- associated risk for major birth defects and miscarriage. There are risks to the mother and fetus associated with poorly controlled diabetes in pregnancy [see Clinical Considerations]. No adverse developmental effects were observed when sitagliptin was administered to pregnant rats and rabbits during organogenesis at oral doses up to 30-times and 20-times, respectively, the 100 mg clinical dose, based on AUC [see Data].
The estimated background risk of major birth defects is 6-10% in women with pre-gestational diabetes with a hemoglobin A1C >7% and has been reported to be as high as 20-25% in women with a hemoglobin A1C >10%. In the U.S. general population, the estimated background risk of major birth defects and miscarriage in clinically recognized pregnancies is 2 to 4% and 15 to 20%, respectively.

Clinical Considerations

Disease-Associated Maternal and/or Embryo/Fetal Risk
Poorly controlled diabetes in pregnancy increases the maternal risk for diabetic ketoacidosis, pre- eclampsia, spontaneous abortions, preterm delivery, and delivery complications. Poorly controlled diabetes increases the fetal risk for major birth defects, still birth, and macrosomia related morbidity.

Data
Animal Data
In embryo-fetal development trials, sitagliptin administered to pregnant rats and rabbits during organogenesis (gestation day 6 to 20) did not adversely affect developmental outcomes at oral doses up to 250 mg/kg (30-times the 100 mg clinical dose) and 125 mg/kg (20-times the 100 mg clinical dose), respectively, based on AUC. Higher doses in rats associated with maternal toxicity increased the incidence of rib malformations in offspring at 1,000 mg/kg, or approximately 100-times the clinical dose, based on AUC. Placental transfer of sitagliptin was observed in pregnant rats and rabbits.
Sitagliptin administered to female rats from gestation day 6 to lactation day 21 caused no functional or behavioral toxicity in offspring of rats at doses up to 1,000 mg/kg.

8.2 Lactation

Risk Summary
There is no information regarding the presence of sitagliptin in human milk, the effects on the breastfed infant, or the effects on milk production. Sitagliptin is present in rat milk and therefore possibly present in human milk [see Data]. The developmental and health benefits of breastfeeding should be considered along with the mother’s clinical need for sitagliptin and any potential adverse effects on the breastfed infant from sitagliptin or from the underlying maternal condition.
Data

Sitagliptin is secreted in the milk of lactating rats at a milk to plasma ratio of 4:1.

8.4 Pediatric Use

The safety and effectiveness of BRYNOVIN have not been established in pediatric patients.
Three 20-week double-blind, placebo-controlled trials each with 34-week extensions were conducted to evaluate the efficacy and safety of sitagliptin in 410 pediatric patients aged 10 to 17 years with inadequately controlled type 2 diabetes mellitus, with or without insulin therapy (HbA1C 6.5-10% for patients not on insulin, HbA1C 7-10% for patients on insulin). At trial entry, patients in trial 1 were not treated with oral antihyperglycemic agents; patients in trials 2 and 3 were on maximally tolerated metformin therapy. The primary efficacy endpoint was the change from baseline in HbA1C after 20 weeks of therapy. The pre-specified primary efficacy analyses included data from trial 1 and pooled data from trials 2 and 3, regardless of glycemic rescue or treatment discontinuation.
In both efficacy analyses, the effect of treatment with sitagliptin was not significantly different from placebo. In trial 1, the mean baseline HbA1C was 7.5%, and 12% of patients were on insulin therapy. At week 20, the change from baseline in HbA1C in patients treated with sitagliptin (N=95) was 0.06% compared to 0.23% in patients treated with placebo (N=95), a difference of -0.17% (95% CI: -0.62, 0.28). In trials 2 and 3, the mean baseline HbA1C was 8%, 15% of patients were on insulin and 72% were on metformin HCl dosages of greater than 1,500 mg daily. At week 20, the change from baseline in HbA1C in patients treated with sitagliptin (N=107) was -0.23% compared to 0.09% in patients treated with placebo (N=113), a difference of -0.33% (95% CI: -0.70, 0.05).

8.5 Geriatric Use

Of the total number of subjects (N=3,884) in pre-approval clinical safety and efficacy trials of sitagliptin, 725 patients were 65 years and over, while 61 patients were 75 years and over. No overall differences in safety or effectiveness have been observed between patients 65 years and over and younger patients.
Because sitagliptin is substantially excreted by the kidney, and because aging can be associated with reduced renal function, renal function should be assessed more frequently in elderly patients [see Dosage and Administration (2.2), Warnings and Precautions (5.3)].

8.6 Renal Impairment

Sitagliptin is excreted by the kidney, and sitagliptin exposure is increased in patients with renal impairment. Lower dosages are recommended in patients with eGFR less than 45 mL/min/1.73 m^2 (moderate and severe renal impairment, as well as in ESRD patients requiring dialysis). [See Dosage and Administration (2.2); Clinical Pharmacology (12.3)].

10 OVERDOSAGE

In the event of an overdose with BRYNOVIN, consider contacting the Poison Help line (1-800-222-1222) or a medical toxicologist for additional overdosage management recommendations. Employ the usual supportive measures dictated by the patient’s clinical status.
Sitagliptin is modestly dialyzable. In clinical trials, approximately 13.5% of the dose was removed over a 3- to 4-hour hemodialysis session. Prolonged hemodialysis may be considered if clinically appropriate. It is not known if sitagliptin is dialyzable by peritoneal dialysis.

11 DESCRIPTION

BRYNOVIN (sitagliptin) oral solution contains sitagliptin hydrochloride (HCl), an orally-active inhibitor of the DPP-4 enzyme.
Sitagliptin HCl is described chemically as ((3R)-3-Amino-1-(3-(trifluoromethy1)-5,6-dihydro-[1,2,4]triazolo[4,3-a]pyrazin-7(8H)-y1)-4-(2,4,5-trifluorophenyl)butan-l-one HCl monohydrate.
The empirical formula is C16H15F6N5O•HCl.H2O and the molecular weight is 461.79. The structural formula is:

Sitagliptin HCl is a white to off-white, crystalline, non-hygroscopic powder. It is soluble in water; very slightly soluble in ethanol; and practically insoluble in n-Heptane.
BRYNOVIN oral solution is a clear, colorless to nearly colorless oral solution. Each mL contains 27.24 mg of sitagliptin HCl, equivalent to 25 mg of sitagliptin. BRYNOVIN contains the following inactive ingredients: butylated hydroxyanisole, citric acid anhydrous, edetate disodium, hydroxyethyl cellulose, methylparaben sodium, polysorbate 80, purified water, sodium citrate dihydrate, and sweetener/flavoring agent.

12 CLINICAL PHARMACOLOGY

12.1 Mechanism of Action

Sitagliptin is a DPP-4 inhibitor, which is believed to exert its actions in patients with type 2 diabetes mellitus by slowing the inactivation of incretin hormones. Concentrations of the active intact hormones are increased by sitagliptin, thereby increasing and prolonging the action of these hormones. Incretin hormones, including glucagon-like peptide-1 (GLP-1) and glucose-dependent insulinotropic polypeptide (GIP), are released by the intestine throughout the day, and levels are increased in response to a meal. These hormones are rapidly inactivated by the enzyme, DPP-4. The incretins are part of an endogenous system involved in the physiologic regulation of glucose homeostasis. When blood glucose concentrations are normal or elevated, GLP-1 and GIP increase insulin synthesis and release from pancreatic beta cells by intracellular signaling pathways involving cyclic AMP. GLP-1 also lowers glucagon secretion from pancreatic alpha cells, leading to reduced hepatic glucose production. By increasing and prolonging active incretin levels, sitagliptin increases insulin release and decreases glucagon levels in the circulation in a glucose-dependent manner. Sitagliptin demonstrates selectivity for DPP-4 and does not inhibit DPP-8 or DPP-9 activity in vitro at concentrations approximating those from therapeutic dosages.

12.2 Pharmacodynamics

General
In patients with type 2 diabetes mellitus, administration of sitagliptin led to inhibition of DPP-4 enzyme activity for a 24-hour period. After an oral glucose load or a meal, this DPP-4 inhibition resulted in a 2- to 3-fold increase in circulating levels of active GLP-1 and GIP, decreased glucagon concentrations, and increased responsiveness of insulin release to glucose, resulting in higher C-peptide and insulin concentrations. The rise in insulin with the decrease in glucagon was associated with lower fasting glucose concentrations and reduced glucose excursion following an oral glucose load or a meal.
In trials with healthy subjects, sitagliptin did not lower blood glucose or cause hypoglycemia.
Sitagliptin and Metformin HCl Coadministration
In a two-day trial in healthy subjects, sitagliptin alone increased active GLP-1 concentrations, whereas metformin alone increased active and total GLP-1 concentrations to similar extents. Coadministration of sitagliptin and metformin had an additive effect on active GLP-1 concentrations. Sitagliptin, but not metformin, increased active GIP concentrations. It is unclear how these findings relate to changes in glycemic control in patients with type 2 diabetes mellitus.
Cardiac Electrophysiology
In a randomized, placebo-controlled crossover trial, 79 healthy subjects were administered a single oral dose of sitagliptin 100 mg, sitagliptin 800 mg (8 times the recommended dose), and placebo. At the recommended dose of 100 mg, there was no effect on the QTc interval obtained at the peak plasma concentration, or at any other time during the trial. Following the 800 mg dose, the maximum increase in the placebo-corrected mean change in QTc from baseline was observed at 3 hours postdose and was 8 msec. This increase is not considered to be clinically significant. At the 800 mg dose, peak sitagliptin plasma concentrations were approximately 11 times higher than the peak concentrations following a 100-mg dose.
In patients with type 2 diabetes mellitus administered sitagliptin 100 mg (N=81) or sitagliptin 200 mg (N=63) daily, there were no meaningful changes in QTc interval based on ECG data obtained at the time of expected peak plasma concentration.

12.3 Pharmacokinetics

The pharmacokinetics of sitagliptin have been extensively characterized in healthy subjects and patients with type 2 diabetes mellitus. Following a single oral 100-mg dose to healthy volunteers, mean plasma AUC of sitagliptin was 8.52 µM•hr, Cmax was 950 nM, and apparent terminal half-life (t1/2) was 12.4 hours. Plasma AUC of sitagliptin increased in a dose-proportional manner and increased approximately 14% following 100 mg doses at steady-state compared to the first dose. The intra-subject and inter-subject coefficients of variation for sitagliptin AUC were small (5.8% and 15.1%). The pharmacokinetics of sitagliptin was generally similar in healthy subjects and in patients with type 2 diabetes mellitus.
Absorption
After oral administration of a 100 mg dose to healthy subjects, sitagliptin was rapidly absorbed with peak plasma concentrations (median Tmax) occurring 1 to 4 hours post dose. The absolute bioavailability of sitagliptin is approximately 87%.
Effect of Food
Administration of 100 mg sitagliptin oral solution with a high-fat meal resulted in similar AUC, ~28.8% decrease in Cmax and 2.5 hour delay in Tmax when compared to the fasted state (Tmax = 1.5 hour). The difference in Cmax and Tmax is not considered clinically meaningful.
Distribution
The mean volume of distribution at steady state following a single 100-mg intravenous dose of sitagliptin to healthy subjects is approximately 198 liters. The fraction of sitagliptin reversibly bound to plasma proteins is low (38%).
Elimination
Approximately 79% of sitagliptin is excreted unchanged in the urine with metabolism being a minor pathway of elimination. The apparent terminal t1/2 following a 100 mg oral dose of sitagliptin was approximately 12.4 hours and renal clearance was approximately 350 mL/min.
Metabolism
Following a [^14C]sitagliptin oral dose, approximately 16% of the radioactivity was excreted as metabolites of sitagliptin. Six metabolites were detected at trace levels and are not expected to contribute to the plasma DPP-4 inhibitory activity of sitagliptin. In vitro trials indicated that the primary enzyme responsible for the limited metabolism of sitagliptin was CYP3A4, with contribution from CYP2C8.
Excretion
Following administration of an oral [^14C]sitagliptin dose to healthy subjects, approximately 100% of the administered radioactivity was eliminated in feces (13%) or urine (87%) within one week of dosing.
Elimination of sitagliptin occurs primarily via renal excretion and involves active tubular secretion. Sitagliptin is a substrate for human organic anion transporter-3 (hOAT-3), which may be involved in the renal elimination of sitagliptin. The clinical relevance of hOAT-3 in sitagliptin transport has not been established. Sitagliptin is also a substrate of P-glycoprotein (P-gp), which may also be involved in mediating the renal elimination of sitagliptin. However, cyclosporine, a P-gp inhibitor, did not reduce the renal clearance of sitagliptin.
Specific Populations
Patients with Renal Impairment
An approximately 2-fold increase in the plasma AUC of sitagliptin was observed in patients with moderate renal impairment with eGFR of 30 to less than 45 mL/min/1.73 m^2, and an approximately 4-fold increase was observed in patients with severe renal impairment, including patients with ESRD on hemodialysis, as compared to normal healthy control subjects.
Patients with Hepatic Impairment
In patients with moderate hepatic impairment (Child-Pugh score 7 to 9), mean AUC and Cmax of sitagliptin increased approximately 21% and 13%, respectively, compared to healthy matched controls following administration of a single 100-mg dose of sitagliptin. These differences are not considered to be clinically meaningful.
There is no clinical experience in patients with severe hepatic impairment (Child-Pugh score >9).
Effects of Age, Body Mass Index (BMI), Gender, and Race
Based on a population pharmacokinetic analysis or a composite analysis of available pharmacokinetic data, BMI, gender, and race do not have a clinically meaningful effect on the pharmacokinetics of sitagliptin. When the effects of age on renal function are taken into account, age alone did not have a clinically meaningful impact on the pharmacokinetics of sitagliptin based on a population pharmacokinetic analysis. Elderly subjects (65 to 80 years) had approximately 19% higher plasma concentrations of sitagliptin compared to younger subjects.
Drug Interaction Studies
In Vitro Assessment of Drug Interactions
Sitagliptin is not an inhibitor of CYP isozymes CYP3A4, 2C8, 2C9, 2D6, 1A2, 2C19 or 2B6, and is not an inducer of CYP3A4. Sitagliptin is a P-gp substrate, but does not inhibit P-gp mediated transport of digoxin. Based on these results, sitagliptin is considered unlikely to cause interactions with other drugs that utilize these pathways.
Sitagliptin is not extensively bound to plasma proteins. Therefore, the propensity of sitagliptin to be involved in clinically meaningful drug-drug interactions mediated by plasma protein binding displacement is very low.

In Vivo Assessment of Drug Interactions
Effects of Sitagliptin on Other Drugs
In clinical trials, sitagliptin did not meaningfully alter the pharmacokinetics of metformin, glyburide, simvastatin, rosiglitazone, digoxin, warfarin, or an oral contraceptive (ethinyl estradiol and norethindrone) (Table 4), providing in vivo evidence of a low propensity for causing drug interactions with substrates of CYP3A4, CYP2C8, CYP2C9, P-gp, and organic cationic transporter (OCT).

Table 4:Effect of Sitagliptin on Systemic Exposure of Coadministered Drugs

Coadministered Drug | Dose of Coadministered Drug* | Dose of Sitagliptin* | Geometric Mean Ratio (ratio with/without sitagliptin) No Effect = 1.00
Coadministered Drug | Dose of Coadministered Drug* | Dose of Sitagliptin* |  | AUC† | Cmax
Digoxin | 0.25 mg‡ once daily for 10 days | 100 mg‡ once daily for 10 days | Digoxin | 1.11§ | 1.18
Glyburide | 1.25 mg | 200 mg‡ once daily for 6 days | Glyburide | 1.09 | 1.01
Simvastatin | 20 mg | 200 mg‡ once daily for 5 days | Simvastatin | 0.85¶ | 0.80
Simvastatin | 20 mg | 200 mg‡ once daily for 5 days | Simvastatin Acid | 1.12¶ | 1.06
Rosiglitazone | 4 mg | 200 mg‡ once daily for 5 days | Rosiglitazone | 0.98 | 0.99
Warfarin | 30 mg single dose on day 5 | 200 mg‡ once daily for 11 days | S(-) Warfarin | 0.95 | 0.89
Warfarin | 30 mg single dose on day 5 | 200 mg‡ once daily for 11 days | R(+) Warfarin | 0.99 | 0.89
Ethinyl estradiol and norethindrone | 21 days once daily of 35 µg ethinyl estradiol with norethindrone 0.5 mg x 7 days, 0.75 mg x 7 days, 1.0 mg x 7 days | 200 mg‡ once daily for 21 days | Ethinyl estradiol | 0.99 | 0.97
Ethinyl estradiol and norethindrone | 21 days once daily of 35 µg ethinyl estradiol with norethindrone 0.5 mg x 7 days, 0.75 mg x 7 days, 1.0 mg x 7 days | 200 mg‡ once daily for 21 days | Norethindrone | 1.03 | 0.98
Metformin HCl | 1,000 mg‡ twice daily for 14 days | 50 mg‡ twice daily for 7 days | Metformin | 1.02# | 0.97

* All doses administered as single dose unless otherwise specified.
† AUC is reported as AUC0-∞ unless otherwise specified.
‡ Multiple dose.
§ AUC0-24hr.
¶ AUC0-last.
# AUC0-12hr.

Effects of Other Drugs on Sitagliptin

Clinical data described below suggest that sitagliptin is not susceptible to clinically meaningful interactions by coadministered medications (Table 5).

Table 5:Effect of Coadministered Drugs on Systemic Exposure of Sitagliptin

Coadministered Drug | Dose of Coadministered Drug* | Dose of Sitagliptin* | Geometric Mean Ratio (ratio with/without coadministered drug) No Effect = 1.00
Coadministered Drug | Dose of Coadministered Drug* | Dose of Sitagliptin* |  | AUC† | Cmax
Cyclosporine | 600 mg once daily | 100 mg once daily | Sitagliptin | 1.29 | 1.68
Metformin HCl | 1,000 mg‡ twice daily for 14 days | 50 mg‡ twice daily for 7 days | Sitagliptin | 1.02§ | 1.05

* All doses administered as single dose unless otherwise specified.
† AUC is reported as AUC0-∞ unless otherwise specified.
‡ Multiple dose.
§ AUC0-12hr.

13 NONCLINICAL TOXICOLOGY

13.1 Carcinogenesis, Mutagenesis, Impairment Of Fertility

A two-year carcinogenicity trial was conducted in male and female rats given oral doses of sitagliptin of 50, 150, and 500 mg/kg/day. There was an increased incidence of combined liver adenoma/carcinoma in males and females and of liver carcinoma in females at 500 mg/kg. This dose results in exposures approximately 60 times the human exposure at the maximum recommended daily adult human dose (MRHD) of 100 mg/day based on AUC comparisons. Liver tumors were not observed at 150 mg/kg, approximately 20 times the human exposure at the MRHD. A two-year carcinogenicity trial was conducted in male and female mice given oral doses of sitagliptin of 50, 125, 250, and 500 mg/kg/day. There was no increase in the incidence of tumors in any organ up to 500 mg/kg, approximately 70 times human exposure at the MRHD. Sitagliptin was not mutagenic or clastogenic with or without metabolic activation in the Ames bacterial mutagenicity assay, a Chinese hamster ovary (CHO) chromosome aberration assay, an in vitro cytogenetics assay in CHO, an in vitro rat hepatocyte DNA alkaline elution assay, and an in vivo micronucleus assay.
In rat fertility trials with oral gavage doses of 125, 250, and 1,000 mg/kg, males were treated for 4 weeks prior to mating, during mating, up to scheduled termination (approximately 8 weeks total) and females were treated 2 weeks prior to mating through gestation day 7. No adverse effect on fertility was observed at 125 mg/kg (approximately 12 times human exposure at the MRHD of 100 mg/day based on AUC comparisons). At higher doses, non-dose-related increased resorptions in females were observed (approximately 25 and 100 times human exposure at the MRHD based on AUC comparison).

14 CLINICAL STUDIES

Overview of Clinical Trials
The effectiveness of BRYNOVIN has been established for glycemic control in patients with type 2 diabetes mellitus based on adequate and well-controlled trials of sitagliptin tablets, referenced below as “sitagliptin”. There were approximately 5,200 patients with type 2 diabetes mellitus randomized in nine double-blind, placebo-controlled clinical safety and efficacy trials conducted to evaluate the effects of sitagliptin on glycemic control. In a pooled analysis of seven of these trials, the ethnic/racial distribution was approximately 59% white, 20% Hispanic or Latino, 10% Asian, 6% Black or African American, and 6% other groups. Patients had an overall mean age of approximately 55 years (range 18 to 87 years). In addition, an active (glipizide)- controlled trial of 52-weeks duration was conducted in 1,172 patients with type 2 diabetes mellitus who had inadequate glycemic control on metformin.
In patients with type 2 diabetes mellitus, treatment with sitagliptin produced clinically significant improvements in hemoglobin A1C, fasting plasma glucose (FPG) and 2-hour post-prandial glucose (PPG) compared to placebo.

14.1 Monotherapy

A total of 1,262 patients with type 2 diabetes mellitus participated in two double-blind, placebo-controlled trials, one of 18-week and another of 24-week duration, to evaluate the efficacy and safety of sitagliptin monotherapy. In both monotherapy trials, patients currently on an antihyperglycemic agent discontinued the agent, and underwent a diet, exercise, and drug washout period of about 7 weeks. Patients with inadequate glycemic control (A1C 7% to 10%) after the washout period were randomized after completing a 2-week single-blind placebo run-in period; patients not currently on antihyperglycemic agents (off therapy for at least 8 weeks) with inadequate glycemic control (A1C 7% to 10%) were randomized after completing the 2-week single-blind placebo run-in period. In the 18-week trial, 521 patients were randomized to placebo, sitagliptin 100 mg, or sitagliptin 200 mg, and in the 24-week trial 741 patients were randomized to placebo, sitagliptin 100 mg, or sitagliptin 200 mg. Patients who failed to meet specific glycemic goals during the trials were treated with metformin rescue, added on to placebo or sitagliptin.
Treatment with sitagliptin at 100 mg daily provided significant improvements in A1C, FPG, and 2-hour PPG compared to placebo (Table 6). In the 18-week trial, 9% of patients receiving sitagliptin 100 mg and 17% who received placebo required rescue therapy. In the 24-week trial, 9% of patients receiving sitagliptin 100 mg and 21% of patients receiving placebo required rescue therapy. The improvement in A1C compared to placebo was not affected by gender, age, race, prior antihyperglycemic therapy, or baseline BMI. In these 18- and 24-week trials, among patients who were not on an antihyperglycemic agent at trial entry, the reductions from baseline in A1C were -0.7% and -0.8%, respectively, for those given sitagliptin, and -0.1% and -0.2%, respectively, for those given placebo. Overall, the 200 mg daily dosage did not provide greater glycemic efficacy than the 100 mg daily dosage. The effect of sitagliptin on lipid endpoints was similar to placebo. Body weight did not increase from baseline with sitagliptin therapy in either trial, compared to a small reduction in patients given placebo.
Table 6:Glycemic Parameters in 18- and 24-Week Placebo-Controlled Trials of Sitagliptin in Adult Patients with Type 2 Diabetes Mellitus*

 | 18-Week Trial |  | 24-Week Trial
 | Sitagliptin 100 mg | Placebo | Sitagliptin 100 mg | Placebo
A1C (%) | N = 193 | N = 103 | N = 229 | N = 244
Baseline (mean) | 8 | 8.1 | 8 | 8
Change from baseline (adjusted mean†) | -0.5 | 0.1 | -0.6 | 0.2
Difference from placebo (adjusted mean†) (95% CI) | -0.6‡ (-0.8, -0.4) |  | -0.8‡ (-1.0, -0.6)
Patients (%) achieving A1C <7% | 69 (36%) | 16 (16%) | 93 (41%) | 41 (17%)
FPG (mg/dL) | N = 201 | N = 107 | N = 234 | N = 247
Baseline (mean) | 180 | 184 | 170 | 176
Change from baseline (adjusted mean†) | -13 | 7 | -12 | 5
Difference from placebo (adjusted mean†) (95% CI) | -20‡ (-31, -9) |  | -17‡ (-24, -10)
2-hour PPG (mg/dL) | § | § | N = 201 | N = 204
Baseline (mean) |  |  | 257 | 271
Change from baseline (adjusted mean†) |  |  | -49 | -2
Difference from placebo (adjusted mean†) (95% CI) |  |  | -47‡ (-59, -34)

* Intent-to-treat population using last observation on trial prior to metformin rescue therapy.
† Least squares means adjusted for prior antihyperglycemic therapy status and baseline value.
‡ p<0.001 compared to placebo.
§ Data not available.
Additional Monotherapy Trial

A multinational, randomized, double-blind, placebo-controlled trial was also conducted to assess the safety and tolerability of sitagliptin in 91 patients with type 2 diabetes mellitus and chronic renal insufficiency (creatinine clearance <50 mL/min). Patients with moderate renal insufficiency received 50 mg daily of sitagliptin and those with severe renal insufficiency or with ESRD on hemodialysis or peritoneal dialysis received 25 mg of sitagliptin daily. In this trial, the safety and tolerability of sitagliptin were generally similar to placebo. A small increase in serum creatinine was reported in patients with moderate renal insufficiency treated with sitagliptin relative to those on placebo. In addition, the reductions in A1C and FPG with sitagliptin compared to placebo were generally similar to those observed in other monotherapy trials. [See Clinical Pharmacology (12.3)].

14.2 Combination Therapy

Add-on Combination Therapy with Metformin
A total of 701 patients with type 2 diabetes mellitus participated in a 24-week, randomized, double-blind, placebo-controlled trial designed to assess the efficacy of sitagliptin in combination with metformin. Patients already on metformin HCl (N=431) at a dosage of at least 1,500 mg per day were randomized after completing a 2-week single-blind placebo run-in period. Patients on metformin and another antihyperglycemic agent (N=229) and patients not on any antihyperglycemic agents (off therapy for at least 8 weeks, N=41) were randomized after a run-in period of approximately 10 weeks on metformin HCl (at a dosage of at least 1,500 mg per day) in monotherapy. Patients with inadequate glycemic control (A1C 7% to 10%) were randomized to the addition of either 100 mg of sitagliptin or placebo, administered once daily. Patients who failed to meet specific glycemic goals during the trials were treated with pioglitazone rescue.
In combination with metformin, sitagliptin provided significant improvements in A1C, FPG, and 2-hour PPG compared to placebo with metformin (Table 7). Rescue glycemic therapy was used in 5% of patients treated with sitagliptin 100 mg and 14% of patients treated with placebo. A similar decrease in body weight was observed for both treatment groups.

Table 7: Glycemic Parameters at Final Visit (24-Week Trial) for Sitagliptin in Add-on Combination Therapy with Metformin in Adult Patients with Type 2 Diabetes Mellitus*

 | Sitagliptin 100 mg + Metformin | Placebo + Metformin
A1C (%) | N = 453 | N = 224
Baseline (mean) | 8 | 8
Change from baseline (adjusted mean†) | -0.7 | -0
Difference from placebo + metformin (adjusted mean†) (95% CI) | -0.7‡ (-0.8, -0.5)
Patients (%) achieving A1C <7% | 213 (47%) | 41 (18%)
FPG (mg/dL) | N = 454 | N = 226
Baseline (mean) | 170 | 174
Change from baseline (adjusted mean†) | -17 | 9
Difference from placebo + metformin (adjusted mean†) (95% CI) | -25‡ (-31, -20)
2-hour PPG (mg/dL) | N = 387 | N = 182
Baseline (mean) | 275 | 272
Change from baseline (adjusted mean†) | -62 | -11
Difference from placebo + metformin (adjusted mean†) (95% CI) | -51‡ (-61, -41)

* Intent-to-treat population using last observation on trial prior to pioglitazone rescue therapy.
† Least squares means adjusted for prior antihyperglycemic therapy and baseline value.
‡ p<0.001 compared to placebo + metformin.

Initial Combination Therapy with Metformin
A total of 1,091 patients with type 2 diabetes mellitus and inadequate glycemic control on diet and exercise participated in a 24-week, randomized, double-blind, placebo-controlled factorial trial designed to assess the efficacy of sitagliptin as initial therapy in combination with metformin. Patients on an antihyperglycemic agent (N=541) discontinued the agent, and underwent a diet, exercise, and drug washout period of up to 12 weeks duration. After the washout period, patients with inadequate glycemic control (A1C 7.5% to 11%) were randomized after completing a 2-week single-blind placebo run-in period. Patients not on antihyperglycemic agents at trial entry (N=550) with inadequate glycemic control (A1C 7.5% to 11%) immediately entered the 2-week single-blind placebo run-in period and then were randomized. Approximately equal numbers of patients were randomized to receive initial therapy with placebo, 100 mg of sitagliptin once daily, 500 mg or 1,000 mg of metformin HCl twice daily, or 50 mg of sitagliptin twice daily in combination with 500 mg or 1,000 mg of metformin HCl twice daily. Patients who failed to meet specific glycemic goals during the trial were treated with glyburide (glibenclamide) rescue.
Initial therapy with the combination of sitagliptin and metformin HCl provided significant improvements in A1C, FPG, and 2-hour PPG compared to placebo, to metformin alone, and to sitagliptin alone (Table 8, Figure 1). Mean reductions from baseline in A1C were generally greater for patients with higher baseline A1C values. For patients not on an antihyperglycemic agent at trial entry, mean reductions from baseline in A1C were: sitagliptin 100 mg once daily, -1.1%; metformin HCl 500 mg bid, -1.1%; metformin HCl 1,000 mg bid, -1.2%; sitagliptin 50 mg bid with metformin HCl 500 mg bid, -1.6%; sitagliptin 50 mg bid with metformin HCl 1,000 mg bid, -1.9%; and for patients receiving placebo, -0.2%. Lipid effects were generally neutral. The decrease in body weight in the groups given sitagliptin in combination with metformin was similar to that in the groups given metformin alone or placebo.

Table 8:Glycemic Parameters at Final Visit (24-Week Trial) for Sitagliptin and Metformin, Alone and in Combination as Initial Therapy in Adult Patients with Type 2 Diabetes Mellitus*

 | Placebo | Sitagliptin 100 mg QD | Metformin HCl 500 mg bid | Metformin HCl 1,000 mg bid | Sitagliptin 50 mg bid + Metformin HCl 500 mg bid | Sitagliptin 50 mg bid + Metformin HCl 1,000 mg bid
A1C (%) | N = 165 | N = 175 | N = 178 | N = 177 | N = 183 | N = 178
Baseline (mean) | 8.7 | 8.9 | 8.9 | 8.7 | 8.8 | 8.8
Change from baseline (adjusted mean†) | 0.2 | -0.7 | -0.8 | -1.1 | -1.4 | -1.9
Difference from placebo (adjusted mean†) |  | -0.8‡ | -1‡ | -1.3‡ | -1.6‡ | -2.1‡
(95% CI) |  | (-1.1, -0.6) | (-1.2, -0.8) | (-1.5, -1.1) | (-1.8, -1.3) | (-2.3, -1.8)
Patients (%) achieving A1C <7% | 15 (9%) | 35 (20%) | 41 (23%) | 68 (38%) | 79 (43%) | 118 (66%)
% Patients receiving rescue medication | 32 | 21 | 17 | 12 | 8 | 2
FPG (mg/dL) | N = 169 | N = 178 | N = 179 | N = 179 | N = 183 | N = 180
Baseline (mean) | 196 | 201 | 205 | 197 | 204 | 197
Change from baseline (adjusted mean†) | 6 | -17 | -27 | -29 | -47 | -64
Difference from placebo (adjusted mean†) |  | -23‡ | -33‡ | -35‡ | -53‡ | -70‡
(95% CI) |  | (-33, -14) | (-43, -24) | (-45, -26) | (-62, -43) | (-79, -60)
2-hour PPG (mg/dL) | N = 129 | N = 136 | N = 141 | N = 138 | N = 147 | N = 152
Baseline (mean) | 277 | 285 | 293 | 283 | 292 | 287
Change from baseline (adjusted mean†) | 0 | -52 | -53 | -78 | -93 | -117
Difference from placebo (adjusted mean†) |  | -52‡ | -54‡ | -78‡ | -93‡ | -117‡
(95% CI) |  | (-67, -37) | (-69, -39) | (-93, -63) | (-107, -78) | (-131, -102)

* Intent-to-treat population using last observation on trial prior to glyburide (glibenclamide) rescue therapy.
† Least squares means adjusted for prior antihyperglycemic therapy status and baseline value.
‡ p<0.001 compared to placebo.

Figure 1: Mean Change from Baseline for A1C (%) over 24 Weeks with Sitagliptin and Metformin, Alone and in Combination as Initial Therapy in Adult Patients with Type 2 Diabetes Mellitus*

Initial combination therapy or maintenance of combination therapy may not be appropriate for all patients. These management options are left to the discretion of the health care provider.

Active-Controlled Trial vs Glipizide in Combination with Metformin
The efficacy of sitagliptin was evaluated in a 52-week, double-blind, glipizide-controlled noninferiority trial in patients with type 2 diabetes mellitus. Patients not on treatment or on other antihyperglycemic agents entered a run-in treatment period of up to 12 weeks duration with metformin HCl monotherapy (dosage of ≥1,500 mg per day) which included washout of medications other than metformin, if applicable. After the run-in period, those with inadequate glycemic control (A1C 6.5% to 10%) were randomized 1:1 to the addition of sitagliptin 100 mg once daily or glipizide for 52 weeks. Patients receiving glipizide were given an initial dosage of 5 mg/day and then electively titrated over the next 18 weeks to a maximum dosage of 20 mg/day as needed to optimize glycemic control. Thereafter, the glipizide dosage was to be kept constant, except for down-titration to prevent hypoglycemia. The mean dosage of glipizide after the titration period was 10 mg.
After 52 weeks, sitagliptin and glipizide had similar mean reductions from baseline in A1C in the intent-to-treat analysis (Table 9). These results were consistent with the per protocol analysis (Figure 2). A conclusion in favor of the non-inferiority of sitagliptin to glipizide may be limited to patients with baseline A1C comparable to those included in the trial (over 70% of patients had baseline A1C <8% and over 90% had A1C <9%).

Table 9: Glycemic Parameters in a 52-Week Trial Comparing Sitagliptin to Glipizide as Add-On Therapy in Adult Patients with Type 2 Diabetes Mellitus Inadequately Controlled on Metformin (Intent-to-Treat Population)*

 | Sitagliptin 100 mg | Glipizide
A1C (%) | N = 576 | N = 559
Baseline (mean) | 7.7 | 7.6
Change from baseline (adjusted mean†) | -0.5 | -0.6
FPG (mg/dL) | N = 583 | N = 568
Baseline (mean) | 166 | 164
Change from baseline (adjusted mean†) | -8 | -8

* The intent-to-treat analysis used the patients’ last observation in the trial prior to discontinuation.
† Least squares means adjusted for prior antihyperglycemic therapy status and baseline A1C value.

Figure 2: Mean Change from Baseline for A1C (%) Over 52 Weeks in a Trial Comparing Sitagliptin to Glipizide as Add-On Therapy in Adult Patients with Type 2 Diabetes Mellitus Inadequately Controlled on Metformin (Per Protocol Population)*

* The per protocol population (mean baseline A1C of 7.5%) included patients without major protocol violations who had observations at baseline and at Week 52.

The incidence of hypoglycemia in the sitagliptin group (4.9%) was significantly (p<0.001) lower than that in the glipizide group (32%). Patients treated with sitagliptin exhibited a significant mean decrease from baseline in body weight compared to a significant weight gain in patients administered glipizide (-1.5 kg vs +1.1 kg).

Add-on Combination Therapy with Pioglitazone
A total of 353 patients with type 2 diabetes mellitus participated in a 24-week, randomized, double-blind, placebo-controlled trial designed to assess the efficacy of sitagliptin in combination with pioglitazone. Patients on any oral antihyperglycemic agent in monotherapy (N=212) or on a PPARγ agent in combination therapy (N=106) or not on an antihyperglycemic agent (off therapy for at least 8 weeks, N=34) were switched to monotherapy with pioglitazone (at a dosage of 30-45 mg per day) and completed a run-in period of approximately 12 weeks in duration. After the run-in period on pioglitazone monotherapy, patients with inadequate glycemic control (A1C 7% to 10%) were randomized to the addition of either 100 mg of sitagliptin or placebo, administered once daily. Patients who failed to meet specific glycemic goals during the trials were treated with metformin rescue. Glycemic endpoints measured were A1C and fasting glucose.
In combination with pioglitazone, sitagliptin provided significant improvements in A1C and FPG compared to placebo with pioglitazone (Table 10). Rescue therapy was used in 7% of patients treated with sitagliptin 100 mg and 14% of patients treated with placebo. There was no significant difference between sitagliptin and placebo in body weight change.

Table 10: Glycemic Parameters at Final Visit (24-Week Trial) for Sitagliptin in Add-on Combination Therapy with Pioglitazone in Adult Patients with Type 2 Diabetes Mellitus*

 | Sitagliptin 100 mg + Pioglitazone | Placebo + Pioglitazone
A1C (%) | N = 163 | N = 174
Baseline (mean) | 8.1 | 8
Change from baseline (adjusted mean†) | -0.9 | -0.2
Difference from placebo + pioglitazone (adjusted mean†) (95% CI) | -0.7‡ (-0.9, -0.5)
Patients (%) achieving A1C <7% | 74 (45%) | 40 (23%)
FPG (mg/dL) | N = 163 | N = 174
Baseline (mean) | 168 | 166
Change from baseline (adjusted mean†) | -17 | 1
Difference from placebo + pioglitazone (adjusted mean†) (95% CI) | -18‡ (-24, -11)

* Intent-to-treat population using last observation on trial prior to metformin rescue therapy.
† Least squares means adjusted for prior antihyperglycemic therapy status and baseline value.
‡ p<0.001 compared to placebo + pioglitazone.

Initial Combination Therapy with Pioglitazone

A total of 520 patients with type 2 diabetes mellitus and inadequate glycemic control on diet and exercise participated in a 24-week, randomized, double-blind trial designed to assess the efficacy of sitagliptin as initial therapy in combination with pioglitazone. Patients not on antihyperglycemic agents at trial entry (<4 weeks cumulative therapy over the past 2 years, and with no treatment over the prior 4 months) with inadequate glycemic control (A1C 8% to 12%) immediately entered the 2-week single-blind placebo run-in period and then were randomized. Approximately equal numbers of patients were randomized to receive initial therapy with 100 mg of sitagliptin in combination with 30 mg of pioglitazone once daily or 30 mg of pioglitazone once daily as monotherapy. There was no glycemic rescue therapy in this trial.
Initial therapy with the combination of sitagliptin and pioglitazone provided significant improvements in A1C, FPG, and 2-hour PPG compared to pioglitazone monotherapy (Table 11). The improvement in A1C was generally consistent across subgroups defined by gender, age, race, baseline BMI, baseline A1C, or duration of disease. In this trial, patients treated with sitagliptin in combination with pioglitazone had a mean increase in body weight of 1.1 kg compared to pioglitazone alone (3 kg vs. 1.9 kg). Lipid effects were generally neutral.

Table 11: Glycemic Parameters at Final Visit (24-Week Trial) for Sitagliptin in Combination with Pioglitazone as Initial Therapy in Adult Patients with Type 2 Diabetes Mellitus*

 | Sitagliptin 100 mg + Pioglitazone | Pioglitazone
A1C (%) | N = 251 | N = 246
Baseline (mean) | 9.5 | 9.4
Change from baseline (adjusted mean†) | -2.4 | -1.5
Difference from pioglitazone (adjusted mean†) (95% CI) | -0.9‡ (-1.1, -0.7)
Patients (%) achieving A1C <7% | 151 (60%) | 68 (28%)
FPG (mg/dL) | N = 256 | N = 253
Baseline (mean) | 203 | 201
Change from baseline (adjusted mean†) | -63 | -40
Difference from pioglitazone (adjusted mean†) (95% CI) | -23‡ (-30, -15)
2-hour PPG (mg/dL) | N = 216 | N = 211
Baseline (mean) | 283 | 284
Change from baseline (adjusted mean†) | -114 | -69
Difference from pioglitazone (adjusted mean†) (95% CI) | -45‡ (-57, -32)

* Intent-to-treat population using last observation on trial.
† Least squares means adjusted for baseline value.
‡ p<0.001 compared to placebo + pioglitazone.

Add-on Combination Therapy with Metformin and Rosiglitazone
A total of 278 patients with type 2 diabetes mellitus participated in a 54-week, randomized, double-blind, placebo-controlled trial designed to assess the efficacy of sitagliptin in combination with metformin and rosiglitazone. Patients on dual therapy with metformin HCl ≥1,500 mg/day and rosiglitazone ≥4 mg/day or with metformin HCl ≥1,500 mg/day and pioglitazone ≥30 mg/day (switched to rosiglitazone ≥4 mg/day) entered a dose-stable run-in period of 6 weeks. Patients on other dual therapy were switched to metformin HCl ≥1,500 mg/day and rosiglitazone ≥4 mg/day in a dosage titration/stabilization run-in period of up to 20 weeks in duration. After the run-in period, patients with inadequate glycemic control (A1C 7.5% to 11%) were randomized 2:1 to the addition of either 100 mg of sitagliptin or placebo, administered once daily. Patients who failed to meet specific glycemic goals during the trial were treated with glipizide (or other sulfonylurea) rescue. The primary time point for evaluation of glycemic parameters was Week 18.
In combination with metformin and rosiglitazone, sitagliptin provided significant improvements in A1C, FPG, and 2-hour PPG compared to placebo with metformin and rosiglitazone (Table 12) at Week 18. At Week 54, mean reduction in A1C was -1% for patients treated with sitagliptin and -0.3% for patients treated with placebo in an analysis based on the intent-to-treat population. Rescue therapy was used in 18% of patients treated with sitagliptin 100 mg and 40% of patients treated with placebo. There was no significant difference between sitagliptin and placebo in body weight change.

Table 12: Glycemic Parameters at Week 18 for Sitagliptin in Add-on Combination Therapy with Metformin and Rosiglitazone in Adult Patients with Type 2 Diabetes Mellitus*

 | Sitagliptin 100 mg + Metformin + Rosiglitazone | Placebo + Metformin + Rosiglitazone
A1C (%) | N = 176 | N = 93
Baseline (mean) | 8.8 | 8.7
Change from baseline (adjusted mean†) | -1 | -0.4
Difference from placebo + rosiglitazone + metformin (adjusted mean†) (95% CI) | -0.7‡ (-0.9, -0.4)
Patients (%) achieving A1C <7% | 39 (22%) | 9 (10%)
FPG (mg/dL) | N = 179 | N = 94
Baseline (mean) | 181 | 182
Change from baseline (adjusted mean†) | -30 | -11
Difference from placebo + rosiglitazone + metformin (adjusted mean†) (95% CI) | -18‡ (-26, -10)
2-hour PPG (mg/dL) | N = 152 | N = 80
Baseline (mean) | 256 | 248
Change from baseline (adjusted mean†) | -59 | -21
Difference from placebo + rosiglitazone + metformin (adjusted mean†) (95% CI) | -39‡ (-51, -26)

* Intent-to-treat population using last observation on trial prior to glipizide (or other sulfonylurea) rescue therapy.
† Least squares means adjusted for prior antihyperglycemic therapy status and baseline value.
‡ p<0.001 compared to placebo + metformin + rosiglitazone.

Add-on Combination Therapy with Glimepiride, with or without Metformin
A total of 441 patients with type 2 diabetes mellitus participated in a 24-week, randomized, double-blind, placebo-controlled trial designed to assess the efficacy of sitagliptin in combination with glimepiride, with or without metformin. Patients entered a run-in treatment period on glimepiride (≥4 mg per day) alone or glimepiride in combination with metformin HCl (≥1,500 mg per day). After a dosage-titration and dosage-stable run-in period of up to 16 weeks and a 2-week placebo run-in period, patients with inadequate glycemic control (A1C 7.5% to 10.5%) were randomized to the addition of either 100 mg of sitagliptin or placebo, administered once daily. Patients who failed to meet specific glycemic goals during the trials were treated with pioglitazone rescue.
In combination with glimepiride, with or without metformin, sitagliptin provided significant improvements in A1C and FPG compared to placebo (Table 13). In the entire trial population (patients on sitagliptin in combination with glimepiride and patients on sitagliptin in combination with glimepiride and metformin), a mean reduction from baseline relative to placebo in A1C of -0.7% and in FPG of -20 mg/dL was seen. Rescue therapy was used in 12% of patients treated with sitagliptin 100 mg and 27% of patients treated with placebo. In this trial, patients treated with sitagliptin had a mean increase in body weight of 1.1 kg vs. placebo (+0.8 kg vs. -0.4 kg). In addition, there was an increased rate of hypoglycemia. [See Warnings and Precautions (5.4); Adverse Reactions (6.1)].

Table 13:Glycemic Parameters at Final Visit (24-Week Trial) for Sitagliptin as Add-On Combination Therapy with Glimepiride, with or without Metformin in Adult Patients with Type 2 Diabetes Mellitus*

 | Sitagliptin 100 mg + Glimepiride | Placebo + Glimepiride | Sitagliptin 100 mg + Glimepiride + Metformin | Placebo + Glimepiride + Metformin
A1C (%) | N = 102 | N = 103 | N = 115 | N = 105
Baseline (mean) | 8.4 | 8.5 | 8.3 | 8.3
Change from baseline (adjusted mean†) | -0.3 | 0.3 | -0.6 | 0.3
Difference from placebo (adjusted mean†) (95% CI) | -0.6‡ (-0.8, -0.3) |  | -0.9‡ (-1.1, -0.7)
Patients (%) achieving A1C <7% | 11 (11%) | 9 (9%) | 26 (23%) | 1 (1%)
FPG (mg/dL) | N = 104 | N = 104 | N = 115 | N = 109
Baseline (mean) | 183 | 185 | 179 | 179
Change from baseline (adjusted mean†) | -1 | 18 | -8 | 13
Difference from placebo (adjusted mean†) (95% CI) | -19§ (-32, -7) |  | -21‡ (-32, -10)

* Intent-to-treat population using last observation on trial prior to pioglitazone rescue therapy.
† Least squares means adjusted for prior antihyperglycemic therapy status and baseline value.
‡ p<0.001 compared to placebo.
§ p<0.01 compared to placebo.

Add-on Combination Therapy with Insulin (with or without Metformin)
A total of 641 patients with type 2 diabetes mellitus participated in a 24-week, randomized, double-blind, placebo-controlled trial designed to assess the efficacy of sitagliptin as add-on to insulin therapy (with or without metformin). The racial distribution in this trial was approximately 70% white, 18% Asian, 7% Black or African American, and 5% other groups. Approximately 14% of the patients in this trial were Hispanic or Latino. Patients entered a 2- week, single-blind run-in treatment period on pre-mixed, long-acting, or intermediate-acting insulin, with or without metformin HCl (≥1,500 mg per day). Patients using short-acting insulins were excluded unless the short-acting insulin was administered as part of a pre-mixed insulin. After the run-in period, patients with inadequate glycemic control (A1C 7.5% to 11%) were randomized to the addition of either 100 mg of sitagliptin or placebo, administered once daily. Patients were on a stable dosage of insulin prior to enrollment with no changes in insulin dosage permitted during the run-in period. Patients who failed to meet specific glycemic goals during the double-blind treatment period were to have uptitration of the background insulin dosage as rescue therapy.
The median daily insulin dosage at baseline was 42 units in the patients treated with sitagliptin and 45 units in the placebo-treated patients. The median change from baseline in daily dosage of insulin was zero for both groups at the end of the trial. In combination with insulin (with or without metformin), sitagliptin provided significant improvements in A1C, FPG, and 2-hour PPG compared to placebo (Table 14). Both treatment groups had an adjusted mean increase in body weight of 0.1 kg from baseline to Week 24. There was an increased rate of hypoglycemia in patients treated with sitagliptin. [See Warnings and Precautions (5.4); Adverse Reactions (6.1)].

Table 14: Glycemic Parameters at Final Visit (24-Week Trial) for Sitagliptin as Add-on Combination Therapy with Insulin in Adult Patients with Type 2 Diabetes Mellitus*

 | Sitagliptin 100 mg + Insulin (+/- Metformin) | Placebo + Insulin (+/- Metformin)
A1C (%) | N = 305 | N = 312
Baseline (mean) | 8.7 | 8.6
Change from baseline (adjusted mean†) | -0.6 | -0.1
Difference from placebo (adjusted mean†,‡) (95% CI) | -0.6§ (-0.7, -0.4)
Patients (%) achieving A1C <7% | 39 (12.8%) | 16 (5.1%)
FPG (mg/dL) | N = 310 | N = 313
Baseline (mean) | 176 | 179
Change from baseline (adjusted mean†) | -18 | -4
Difference from placebo (adjusted mean†) (95% CI) | -15§ (-23, -7)
2-hour PPG (mg/dL) | N = 240 | N = 257
Baseline (mean) | 291 | 292
Change from baseline (adjusted mean†) | -31 | 5
Difference from placebo (adjusted mean†) (95% CI) | -36§ (-47, -25)

* Intent-to-treat population using last observation on trial prior to rescue therapy.
† Least squares means adjusted for metformin use at the screening visit (yes/no), type of insulin used at the screening visit (pre- mixed vs. non-pre-mixed [intermediate- or long-acting]), and baseline value.
‡ Treatment by stratum interaction was not significant (p>0.10) for metformin stratum and for insulin stratum.
§ p<0.001 compared to placebo.

Maintenance of BRYNOVIN During Initiation and Titration of Insulin Glargine
A total of 746 patients with type 2 diabetes mellitus (mean baseline HbA1C 8.8%, disease duration 10.8 years) participated in a 30-week, randomized, double-blind, placebo-controlled trial to assess the efficacy and safety of continuing sitagliptin during the initiation and up- titration of insulin glargine. Patients who were on a stable dosage of metformin HCl (≥1,500 mg/day) in combination with a DPP-4 inhibitor and/or sulfonylurea but with inadequate glycemic control (A1C 7.5% to 11%) were enrolled in the trial. Those on metformin and sitagliptin (100 mg/day) directly entered the double-blind treatment period; those on another DPP-4 inhibitor and/or on a sulfonylurea entered a 4–8-week run-in period in which they were maintained on metformin and switched to sitagliptin (100 mg); other DPP-4 inhibitors and sulfonylureas were discontinued. At randomization patients were randomized either to continue sitagliptin or to discontinue sitagliptin and switch to a matching placebo. On the day of randomization, insulin glargine was initiated at a dosage of 10 units subcutaneously in the evening. Patients were instructed to uptitrate their insulin dosage in the evening based on fasting blood glucose measurements to achieve a target of 72-100 mg/dL.
At 30 weeks, the mean reduction in A1C was greater in the sitagliptin group than in the placebo group (Table 15). At the end of the trial, 27.3% of patients in the sitagliptin group and 27.3% in the placebo group had a fasting plasma glucose (FPG) in the target range; there was no significant difference in insulin dosage between arms.

Table 15: Change from Baseline in A1C and FPG at Week 30 in the Maintenance of Sitagliptin During Initiation and Titration of Insulin Glargine Trial

 | Sitagliptin 100 mg +Metformin + Insulin Glargine | Placebo +Metformin + Insulin Glargine
A1C (%) | N = 373† | N = 370†
Baseline (mean) | 8.8 | 8.8
Week 30 (mean) | 6.9 | 7.3
Change from baseline (adjusted mean) * | -1.9 | -1.4
Difference from placebo (adjusted mean) (95% CI) * | -0.4 (-0.6, -0.3) ‡
Patients (%) with A1C <7% | 202 (54.2%) | 131 (35.4%)
FPG (mg/dL) | N = 373† | N = 370†
Baseline (mean) | 199 | 201
Week 30 (mean) | 118 | 123
Change from baseline (adjusted mean) * | -81 | -76

*Analysis of Covariance including all post-baseline data regardless of rescue or treatment discontinuation. Model estimates calculated using multiple imputation to model washout of the treatment effect using placebo data for all subjects having missing Week 30 data.
†N is the number of randomized and treated patients.
‡p<0.001 compared to placebo.

16 HOW SUPPLIED/STORAGE AND HANDLING

BRYNOVIN (sitagliptin) oral solution 25 mg/mL is supplied as a clear colorless, to nearly colorless aqueous solution in an amber glass bottle with a child resistant closure.
Each bottle contains 120 mL oral solution, NDC 24338-017-01
Storage
Store refrigerated at 2°C to 8°C (36°F to 46°F) [see USP]; Protect from light. Avoid excessive heat and freezing. Discard unused portion 90 days after first opening.

17 PATIENT COUNSELING INFORMATION

Advise the patient to read the FDA-approved patient labeling (Medication Guide).
Dosage and Administration
Instruct patients or caregivers to use an oral dosing syringe or oral dosing cup to correctly measure the prescribed amount of medication. Inform patients that oral dosing syringes and cups may be obtained from their pharmacy [see Dosage and Administration (2.1)].

Pancreatitis
Inform patients that acute pancreatitis has been reported during postmarketing use of sitagliptin. Inform patients that persistent severe abdominal pain, sometimes radiating to the back, which may or may not be accompanied by vomiting, is the hallmark symptom of acute pancreatitis. Instruct patients to promptly discontinue BRYNOVIN and contact their physician if persistent severe abdominal pain occurs [see Warnings and Precautions (5.1)].

Heart Failure
Inform patients of the signs and symptoms of heart failure. Before initiating BRYNOVIN, ask patients about a history of heart failure or other risk factors for heart failure including moderate to severe renal impairment. Instruct patients to contact their health care provider as soon as possible if they experience symptoms of heart failure, including increasing shortness of breath, rapid increase in weight or swelling of the feet [see Warnings and Precautions (5.2)].
Hypoglycemia with Concomitant Use with Insulin or Insulin Secretagogues
Inform patients that the incidence of hypoglycemia is increased when BRYNOVIN is added to insulin or a sulfonylurea. Explain to patients receiving BRYNOVIN in combination with these medications the risks of hypoglycemia, its symptoms and treatment, and conditions that predispose to its development [see Warnings and Precautions (5.4)].

Hypersensitivity Reactions
Inform patients that allergic reactions have been reported during postmarketing use of sitagliptin. If symptoms of allergic reactions (including rash, hives, and swelling of the face, lips, tongue, and throat that may cause difficulty in breathing or swallowing) occur, patients must stop taking BRYNOVIN and seek medical advice promptly [see Warnings and Precautions (5.5)].

Severe and Disabling Arthralgia
Inform patients that severe and disabling joint pain may occur with this class of drugs. The time to onset of symptoms can range from one day to years. Instruct patients to seek medical advice if severe joint pain occurs [see Warnings and Precautions (5.6)].

Bullous Pemphigoid
Inform patients that bullous pemphigoid may occur with this class of drugs. Instruct patients to seek medical advice if blisters or erosions occur [see Warnings and Precautions (5.7)].

Manufactured for:
Azurity Pharmaceuticals, Inc.
Woburn, MA 01801

BRYNOVIN is a registered trademark of Azurity Pharmaceuticals, Inc.
For patent information: https://azurity.com/patents.
This products labeling may have been updated. For current Full Prescribing Information, please visit www.BRYNOVIN.com
PN: BRY-PI-00

SPL MEDGUIDE SECTION

Medication Guide
BRYNOVINTM (bri-know-vin)
(sitagliptin)
oral solution

What is the most important information I should know about BRYNOVIN?
BRYNOVIN can cause serious side effects, including:
• Inflammation of the pancreas (pancreatitis) which may be severe and lead to death. Certain medical problems make you more likely to get pancreatitis.
Before you start taking BRYNOVIN, tell your healthcare provider if you have ever had:
• Pancreatitis
• stones in your gallbladder (gallstones)
• a history of alcoholism
• high blood triglyceride levels
• kidney problems
Stop taking BRYNOVIN and call your healthcare provider right away if you have pain in your stomach area (abdomen) that is severe and will not go away. The pain may be felt going from your abdomen through to your back. The pain may happen with or without vomiting. These may be symptoms of pancreatitis.
• Heart failure. Heart failure means your heart does not pump blood well enough.
Before you start taking BRYNOVIN, tell your healthcare provider if you have ever had heart failure or have problems with your kidneys. Contact your healthcare provider right away if you have any of the following symptoms:• increasing shortness of breath or trouble breathing, especially when you lie down
• swelling or fluid retention, especially in the feet, ankles or legs
• an unusually fast increase in weight
• unusual tiredness
These may be symptoms of heart failure.

What is BRYNOVIN?
• BRYNOVIN is a prescription medicine used along with diet and exercise to lower blood sugar in adults with type 2 diabetes.
• BRYNOVIN is not for people with type 1 diabetes.
• If you have had pancreatitis (inflammation of the pancreas) in the past, it is not known if you have a higher chance of getting pancreatitis while you take BRYNOVIN.
• It is not known if BRYNOVIN is safe and effective in children.

Who should not take BRYNOVIN?
Do not take BRYNOVIN if:
• you are allergic to sitagliptin or any of the ingredients in BRYNOVIN. See the end of this Medication Guide for a complete list of ingredients in BRYNOVIN.
Symptoms of a serious allergic reaction to BRYNOVIN may include rash, raised red patches on your skin (hives), or swelling of the face, lips, tongue, and throat that may cause difficulty in breathing or swallowing.

What should I tell my healthcare provider before taking BRYNOVIN?
Before you take BRYNOVIN, tell your healthcare provider about all of your medical conditions, including if you:
• have or have had inflammation of your pancreas (pancreatitis).
• have kidney problems.
• have heart failure.
• are pregnant or plan to become pregnant. It is not known if BRYNOVIN will harm your unborn baby. If you are pregnant, talk with your healthcare provider about the best way to control your blood sugar while you are pregnant.
• are breastfeeding or plan to breastfeed. It is not known if BRYNOVIN will pass into your breast milk. Talk with your healthcare provider about the best way to feed your baby if you are taking BRYNOVIN.
Tell your healthcare provider about all the medicines you take, including prescription and over-the-counter medicines, vitamins, and herbal supplements.
Know the medicines you take. Keep a list of your medicines and show it to your healthcare provider and pharmacist when you get a new medicine.

How should I take BRYNOVIN?
• Use an oral dosing syringe or oral dosing cup to correctly measure your dose of BRYNOVIN. Ask your pharmacist for an oral dosing syringe or oral dosing cup if you do not have one.
• Take BRYNOVIN 1 time each day exactly as your healthcare provider tells you.
• You can take BRYNOVIN with or without food.
• Your healthcare provider will do blood tests to check how well your kidneys are working before and during your treatment with BRYNOVIN.
• Your healthcare provider may tell you to take BRYNOVIN along with other diabetes medicines. Low blood sugar can happen more often when BRYNOVIN is taken with certain other diabetes medicines. See “What are the possible side effects of BRYNOVIN?”.
• If you take too much BRYNOVIN, call your healthcare provider or the Poison Help line at 1-800-222-1222 or go to the nearest hospital emergency room right away.

What are the possible side effects of BRYNOVIN?
BRYNOVIN can cause serious side effects, including:
• See "What is the most important information I should know about BRYNOVIN?”
• Kidney problems, sometimes requiring dialysis.
• Low blood sugar (hypoglycemia). If you take BRYNOVIN with another medicine that can cause low blood sugar, such as a sulfonylurea or insulin, your risk of getting low blood sugar is higher. The dose of your sulfonylurea medicine or insulin may need to be lowered while you use BRYNOVIN. Signs and symptoms of low blood sugar may include:
• headache
• irritability
• dizziness
• sweating
• weakness
• drowsiness
• hunger
• confusion
• feeling jittery
• fast heartbeat
• Serious allergic reactions. If you have any symptoms of a serious allergic reaction, stop taking BRYNOVIN and call your healthcare provider right away or get emergency medical help. See “Who should not take BRYNOVIN?”. Your healthcare provider may give you a medicine for your allergic reaction and prescribe a different medicine for your diabetes.
• Joint pain. Some people who take BRYNOVIN, may develop joint pain that can be severe. Call your healthcare provider if you have severe joint pain.• Skin reaction. Some people who take BRYNOVIN may develop a skin reaction called bullous pemphigoid that can require treatment in a hospital. Tell your healthcare provider right away if you develop blisters or the breakdown of the outer layer of your skin (erosion). Your healthcare provider may tell you to stop taking BRYNOVIN.
The most common side effects of BRYNOVIN include upper respiratory infection, stuffy or runny nose and sore throat, and headache.
These are not all the possible side effects of BRYNOVIN. For more information, ask your healthcare provider or pharmacist.
Tell your healthcare provider if you have any side effect that bothers you or does not go away.
Call your doctor for medical advice about side effects. You may report side effects to FDA at 1-800-FDA-1088.
You may also report side effects to Azurity Pharmaceuticals, Inc., at 1-800-461-7449 or www.fda.gov/medwatch.

How should I store BRYNOVIN?
• Store BRYNOVIN in the refrigerator, between 36°F to 46°F (2°C to 8°C).
• Protect BRYNOVIN from light.
• Avoid excessive heat.
• Avoid freezing BRYNOVIN.
• Throw away BRYNOVIN if not used within 90 days after you first open the bottle.
Keep BRYNOVIN and all medicines out of the reach of children.

General information about the safe and effective use of BRYNOVIN.
Medicines are sometimes prescribed for purposes other than those listed in a Medication Guide. Do not use BRYNOVIN for a condition for which it was not prescribed. Do not give BRYNOVIN to other people, even if they have the same symptoms you have. It may harm them.
This Medication Guide summarizes the most important information about BRYNOVIN. If you would like to know more information, talk with your healthcare provider. You can ask your healthcare provider or pharmacist for information about BRYNOVIN that is written for health professionals.

What are the ingredients in BRYNOVIN?
Active ingredient: sitagliptin
Inactive ingredients: butylated hydroxyanisole, citric acid anhydrous, edetate disodium, hydroxyethyl cellulose, methylparaben sodium, polysorbate 80, purified water, sodium citrate dihydrate, and sweetener/flavoring agent.

Manufactured for: Azurity Pharmaceuticals, Inc.
Woburn, MA 01801
BRYNOVIN is a registered trademark of Azurity Pharmaceuticals, Inc.
For patent information: https://azurity.com/patents.
This medication guide may have been updated. For current medication guide, please visit www.BRYNOVIN.com

This Medication Guide has been approved by the U.S. Food and Drug Administration. Issued: 01/2025

PACKAGE LABEL.PRINCIPAL DISPLAY PANEL

BRYNOVIN (Sitagliptin) Oral Solution 25 mg/mL - Carton Label

NDC 24338-017-01

120 mL

Rx only

BRYNOVIN (Sitagliptin) Oral Solution 25 mg/mL - Bottle Label

NDC 24338-017-01

120 mL

Rx only